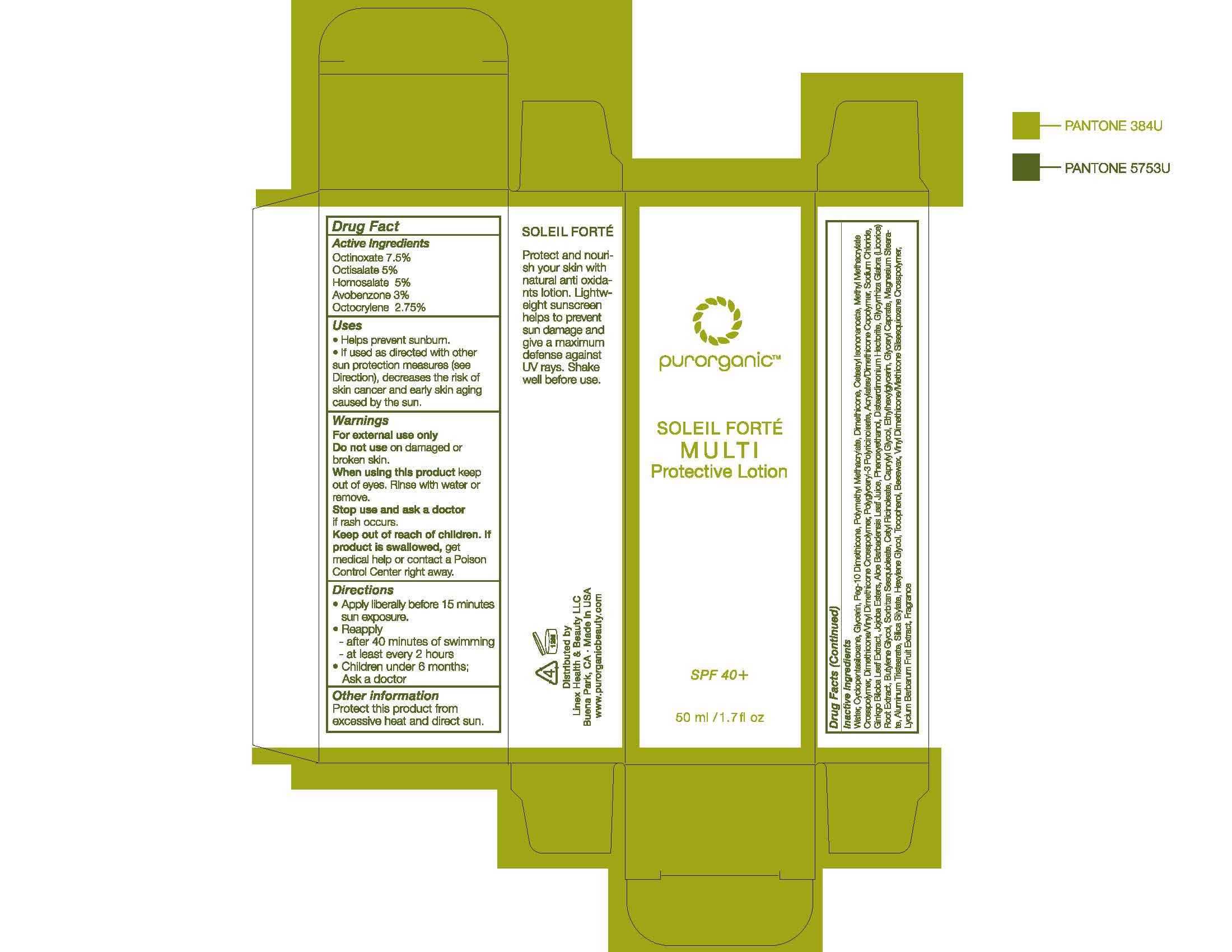 DRUG LABEL: SOLEIL FORTE MULTI
NDC: 69769-101 | Form: LOTION
Manufacturer: LINEX HEALTH & BEAUTY
Category: otc | Type: HUMAN OTC DRUG LABEL
Date: 20221229

ACTIVE INGREDIENTS: HOMOSALATE 5 g/100 mL; OCTINOXATE 7.5 g/100 mL; OCTISALATE 5 g/100 mL; AVOBENZONE 3 g/100 mL; OCTOCRYLENE 2.75 g/100 mL
INACTIVE INGREDIENTS: WATER; .ALPHA.,.BETA.'-DIGLYCERIN; POLYGLYCEROL POLYRICINOLEIC ACID; DIMETHICONE CROSSPOLYMER (450000 MPA.S AT 12% IN CYCLOPENTASILOXANE); SODIUM CHLORIDE; GINKGO BILOBA WHOLE; HYDROGENATED JOJOBA OIL, RANDOMIZED; ALOE VERA LEAF; PHENOXYETHANOL; DISTEARDIMONIUM HECTORITE; GLYCYRRHIZA GLABRA; BUTYLENE GLYCOL; SORBITAN SESQUIOLEATE; CETYL RICINOLEATE; CAPRYLYL GLYCOL; ETHYLHEXYLGLYCERIN; GLYCERYL CAPRATE; MAGNESIUM STEARATE; ALUMINUM STEARATES; SILICA DIMETHYL SILYLATE; HEXYLENE GLYCOL; TOCOPHEROL; YELLOW WAX; POLYMETHYLSILSESQUIOXANE (11 MICRONS); LYCIUM BARBARUM FRUIT; CYCLOMETHICONE 5; PEG-10 DIMETHICONE (600 CST); POLY(METHYL METHACRYLATE; 450000 MW); CETEARYL ISONONANOATE; METHYL METHACRYLATE; DIMETHICONE/VINYL DIMETHICONE CROSSPOLYMER (SOFT PARTICLE)

Linex (as PLD) - SOLEIL FORTE MULTI (67969-101)

ACTIVE INGREDIENT

OCTINOXATE 7.5%

OCTISALATE 5%

HOMOSALATE 5%

AVOBENZONE 3%

OCTOCRYLENE 2.75%

PURPOSE

SUNSCREEN

USES

- HELPS PREVENT SUNBURN.
- IF USED AS DIRECTED WITH OTHER SUN PROTECTION MEASURES (SEE DIRECTIONS), DECREASES THE RISK OF SKIN CANCER AND EARLY SKIN AGING CAUSED BY THE SUN.

WARNINGS

FOR EXTERNAL USE ONLY

DO NOT USE ON DAMAGED OR BROKEN SKIN.

WHEN USING THIS PRODUCT KEEP OUT OF EYES. RINSE WITH WATER TO REMOVE.

STOP USE AND ASK A DOCTOR IF RASH OCCURS.

KEEP OUT OF REACH OF CHILDREN. IF PRODUCT IS SWALLOWED, GET MEDICAL HELP OR CONTACT A POISON CONTROL CENTER RIGHT AWAY.

DIRECTIONS

- APPLY LIBERALLY BEFORE 15 MINUTES SUN EXPOSURE.
- REAPPLY
- AFTER 40 MINUTES OF SWIMMING
- AT LEAST EVERY 2 HOURS
- CHILDREN UNDER 6 MONTHS; ASK A DOCTOR.

OTHER INFORMATION

PROTECT THIS PRODUCT FROM EXCESSIVE HEAT AND DIRECT SUN.

INACTIVE INGREDIENTS

WATER, CYCLOPENTASILOXANE, GLYCERIN, PEG-10 DIMETHICONE, POLYMETHYL METHACRYLATE, DIMETHICONE, CETEARYL ISONONANOATE, METHYL METHACRYLATE CROSSPOLYMER, DIMETHICONE/VINYL DIMETHICONE CROSSPOLYMER, POLYGLYCERYL-3 POLYRICINOLEATE, ACRYLATES/DIMETHICONE COPOLYMER, SODIUM CHLORIDE, GINKGO BILOBA LEAF EXTRACT, JOJOBA ESTERS, ALOE BARBADENSIS LEAF JUICE, PHENOXYETHANOL, DISTEARDIMONIUM HECTORITE, GLYCYRRHIZA GLABRA (LICORICE) ROOT EXTRACT, BUTYLENE GLYCOL, SORBITAN SESQUIOLEATE, CETYL RICINOLEATE, CAPRYLYL GLYCOL, ETHYLHEXYLGLYCERIN, GLYCERYL CAPRATE, MAGNESIUM STEARATE, ALUMINUM TRISTEARATE, SILICA SILYLATE, HEXYLENE GLYCOL, TOCOPHEROL, BEESWAX, VINYL DIMETHICONE/METHICONE SESQUIOXANE CROSSPOLYMER, LYCIUM BARBARUM FRUIT EXTRACT, FRAGRANCE.